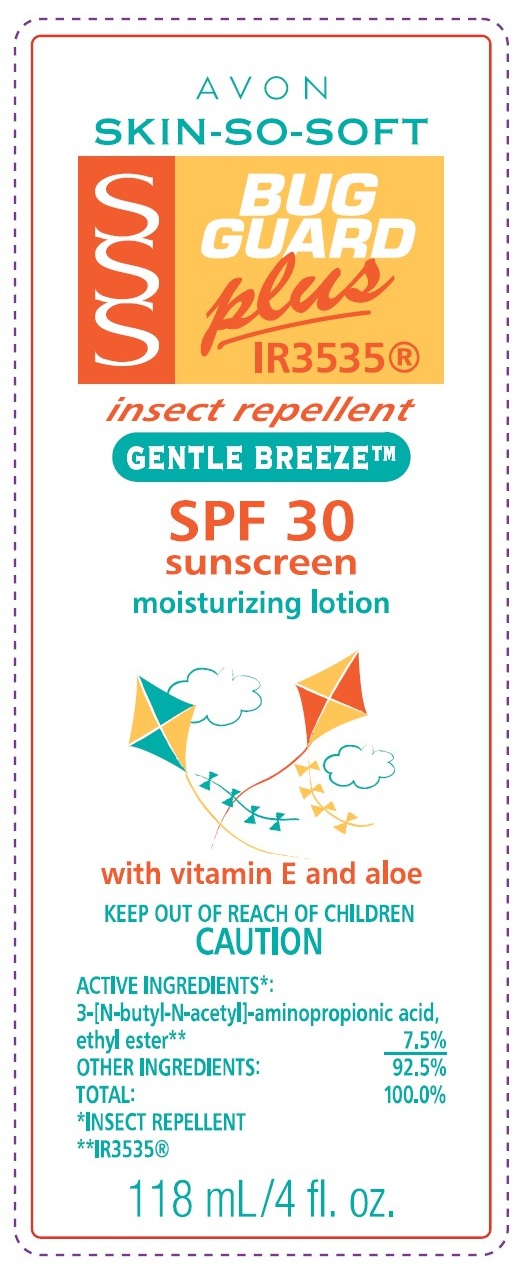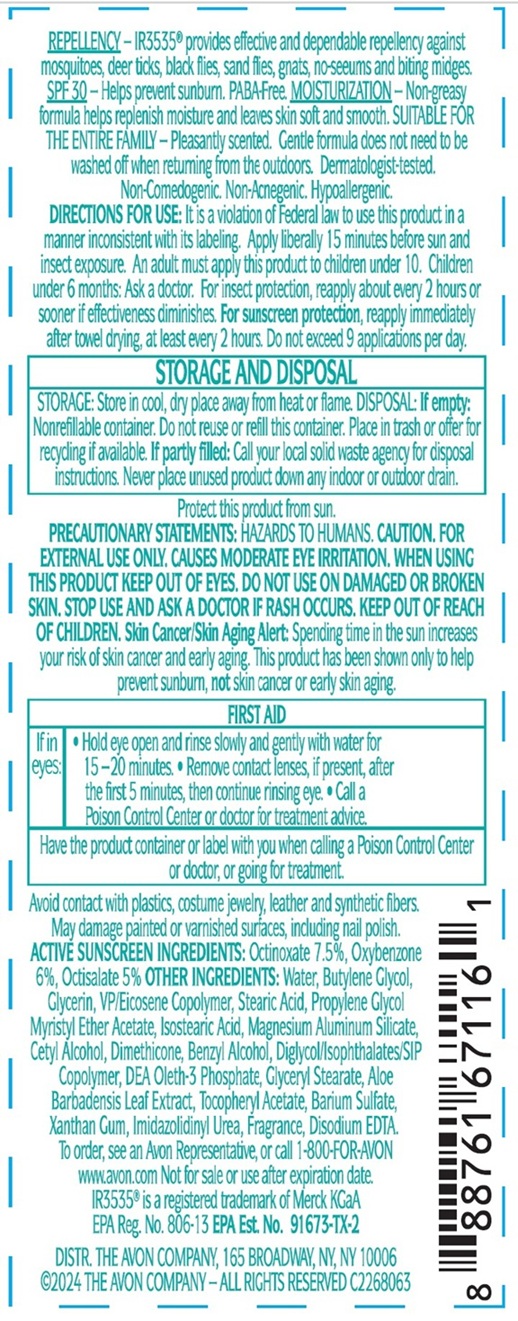 DRUG LABEL: Avon Skin-So-Soft Bug Guard plus SPF 30 Sunscreen
NDC: 10096-8027 | Form: LOTION
Manufacturer: The Avon Company
Category: otc | Type: HUMAN OTC DRUG LABEL
Date: 20250217

ACTIVE INGREDIENTS: OCTINOXATE 7.5 g/1 mL; OXYBENZONE 6 g/1 mL; OCTISALATE 5 g/1 mL
INACTIVE INGREDIENTS: WATER

10096-8027-1 Avon Skin-So-Soft Bug Guard plus Gentle Breeze SPF 30 Sunscreen

INDICATIONS AND USAGE

Helps prevent sunburn.

DOSAGE AND ADMINISTRATION

DIRECTIONS FOR USE: It is a violation of Federal law to use this product in a manner inconsistent with its labeling. Apply liberally 15 minutes before sun and insect exposure. An adult must apply this product to children under 10. Children under 6 months: Ask a doctor. For insect protection, reapply about every 2 hours or sooner if effectiveness diminishes. For sunscreen protection, reapply immediately after towel drying, at least every 2 hours. Do not exceed 9 applications per day.

STORAGE AND HANDLING

STORAGE: Store in cool, dry place away from heat or flame.

Protect this product from sun.

WARNINGS

CAUTION. FOR EXTERNAL USE ONLY. CAUSES MODERATE EYE IRRITATION. WHEN USING THIS PRODUCT KEEP OUT EYES. DO NOT USE ON DAMAGED OR BROKEN SKIN. STOP USE AND ASK A DOCTOR IF RASH OCCURS. KEEP OUR OF REACH OF CHILDREN. Skin Cancer/Skin Aging Alert: Spending time in the sun increases your risk of skin cancer and early aging. This product has been shown only to prevent sunburn, not skin cancer or early skin aging.
If in eyes:

- Hold eye open and rinse slowly and gently with water for 15-20 minutes
- Remove contact lenses if present, after the first 5 minutes, then continue rinsing eye
- Call a Poison Control Center or doctor for treatment advice.

Have the product container or label with you when calling a Poision Control Center or doctor, or going for treament.

KEEP OUR OF REACH OF CHILDREN.

ACTIVE INGREDIENT

ACTIVE SUNSCREEN INGREDIENTS: Octinoxate 7.5%, Oxybenzone 6%, Octisalate 5%

PURPOSE

Sunscreen

INACTIVE INGREDIENT

OTHER INGREDIENTS: Water, Butylene Glycol, Glycerin, VP/Eicosene Copolymer, Stearic Acid, Propylene Glycol Myristyl Ether Acetate, Magnesium Aluminum Silicate, Cetyl Alcohol, Dimethicone, Benzyl Alcohol, Diglycol/Isophthalates/SIP Copolymer, DEA-Oleth-3 Phosphate, Glyceryl Stearate, Aloe Barbadensis Leaf Extract, Tocopheryl Acetate, Barium Sulfate, Xanthan Gum, Imidazolidinyl Urea, Fragrance, Disodium EDTA

QUESTIONS

To order, see an Avon Representative, or call 1-800-FOR-AVON
www.avon.com
DISTR. THE AVON COMPANY, 165 BROADWAY, NY, NY 10006
©2024 THE AVON COMPANY - ALL RIGHTS RESERVED C226806

Principal Display Panel:

AVON
SKIN-SO-SOFT
SSS BUG GUARD
plus IR3535®
insect repellent
GENTLE BREEZE™
SPF 30
sunscreen
moisturizing lotion
with vitamin E and aloe
KEEP OUT OF REACH OF CHILDREN
CAUTION
118 mL / 4 fl. oz.